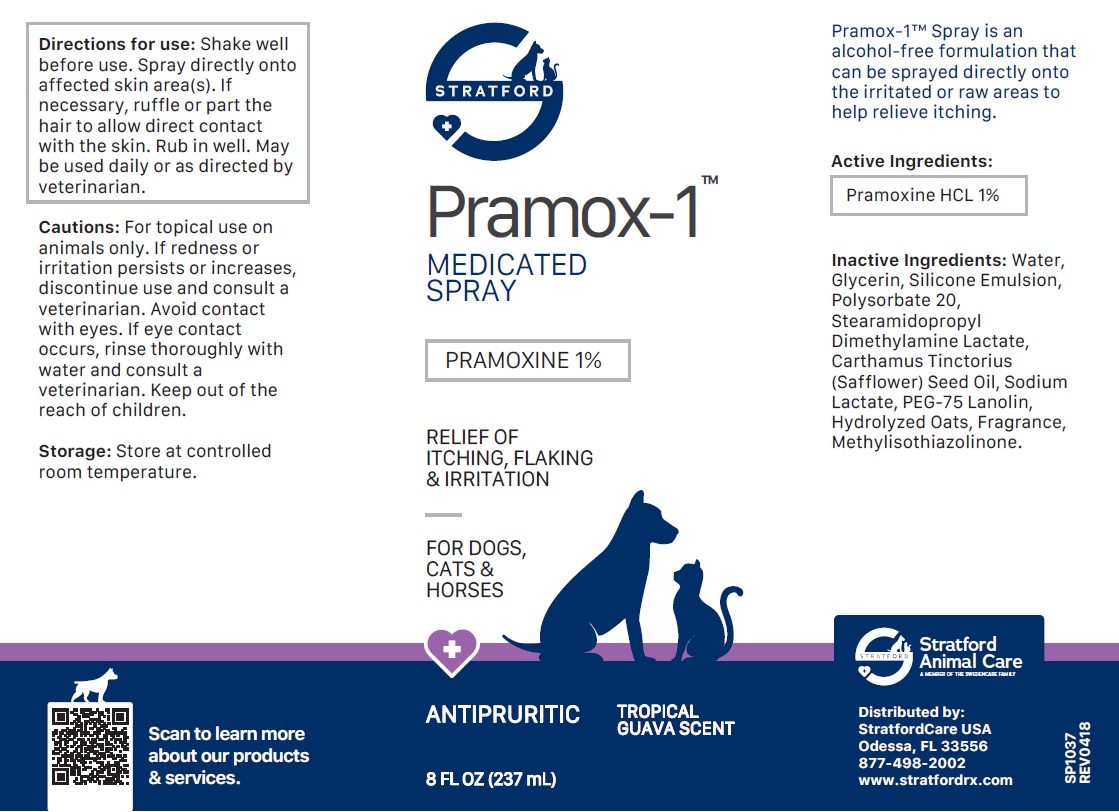 DRUG LABEL: Pramox-1
NDC: 86069-108 | Form: SPRAY
Manufacturer: Stratford Care Usa, Inc.
Category: animal | Type: OTC ANIMAL DRUG LABEL
Date: 20221110

ACTIVE INGREDIENTS: PRAMOXINE HYDROCHLORIDE 1 g/100 mL
INACTIVE INGREDIENTS: WATER; GLYCERIN; POLYSORBATE 20; STEARAMIDOPROPYL DIMETHYLAMINE LACTATE; SAFFLOWER OIL; SODIUM LACTATE; PEG-75 LANOLIN; OAT; METHYLISOTHIAZOLINONE

Pramox-1™ SPRAY

Active Ingredients:

Pramoxine HCL 1%

PURPOSE

ANTIPRURITIC

INDICATIONS AND USAGE

Pramox-1™ Spray is an alcohol-free formulation that can be sprayed directly onto the irritated or raw areas to help relieve itching.

INACTIVE INGREDIENT

Inactive Ingredients: Water, Glycerin, Silicone Emulsion, Polysorbate 20, Stearamidopropyl Dimethylamine Lactate, Carthamus Tinctorius (Safflower) Seed Oil, Sodium Lactate, PEG-75 Lanolin, Hydrolyzed Oats, Fragrance, Methylisothiazolinone.

DOSAGE AND ADMINISTRATION

Directions for use: Shake well before use. Spray directly onto affected skin area(s). If necessary, ruffle or part the hair to allow direct contact with the skin. Rub in well. May be used daily or as directed by veterinarian.

PRECAUTIONS

Cautions: For topical use on animals only. If redness or irritation persists or increases, discontinue use and consult a veterinarian. Avoid contact with eyes. If eye contact occurs, rinse thoroughly with water and consult a veterinarian. Keep out of the reach of children.

Storage: Store at controlled room temperature.

MEDICATED SPRAY

RELIEF OF ITCHING, FLAKING & IRRITATION

FOR DOGS, CATS & HORSES

TROPICAL GUAVA SCENT

Stratford Animal Care
A MEMBER OF THE SWEDENCARE FAMILY

Distributed by:
StratfordCare USA
Odessa, FL 33556
877-498-2002
www.stratfordrx.com